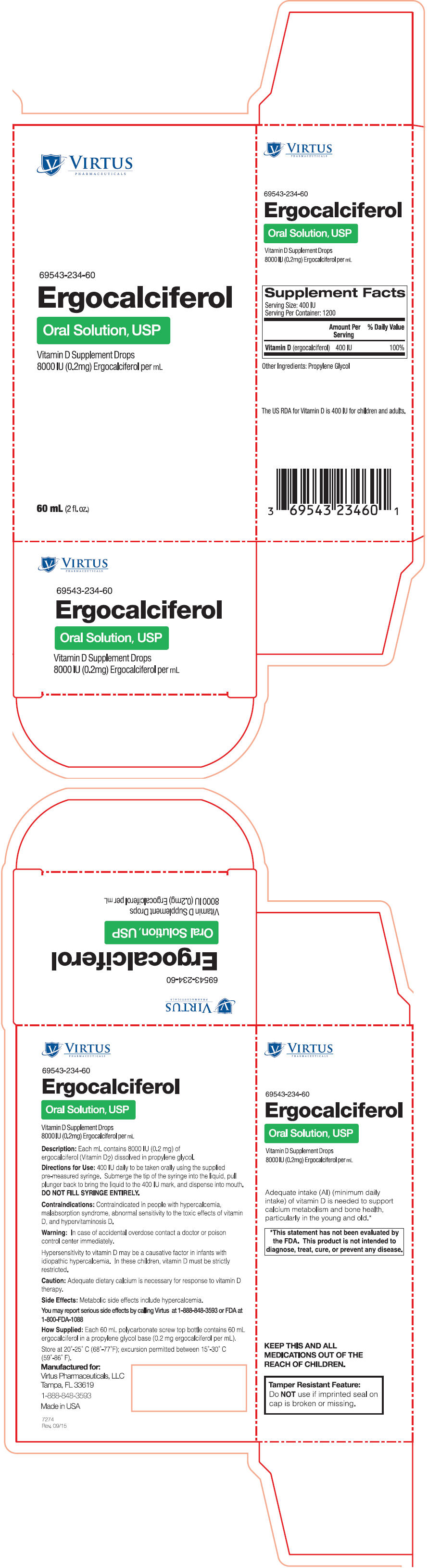 DRUG LABEL: Ergocalciferol
NDC: 69543-234 | Form: LIQUID
Manufacturer: Virtus Pharmaceuticals
Category: other | Type: DIETARY SUPPLEMENT
Date: 20160223

ACTIVE INGREDIENTS: Ergocalciferol 0.2 mg/1 mL
INACTIVE INGREDIENTS: Propylene Glycol

Ergocalciferol
Oral Solution, USP

STATEMENT OF IDENTITY

69543-234-60

Vitamin D Supplement Drops
8000 lU (0.2mg) Ergocalciferol per mL

HEALTH CLAIM

Supplement Facts
Serving Size: 400 IU
Serving Per Container: 1200
 | Amount Per Serving | % Daily Value
Vitamin D (ergocalciferol) | 400 IU | 100%

Other Ingredients: Propylene Glycol

The US RDA for Vitamin D is 400 IU for children and adults.

Description

Each mL contains 8000 IU (0.2 mg) of ergocalciferol (Vitamin D2) dissolved in propylene glycol.

Directions for Use

400 IU daily to be taken orally using the supplied pre-measured syringe. Submerge the tip of the syringe into the liquid, pull plunger back to bring the liquid to the 400 IU mark, and dispense into mouth.

DO NOT FILL SYRINGE ENTIRELY.

Contraindications

Contraindicated in people with hypercalcemia, malabsorption syndrome, abnormal sensitivity to the toxic effects of vitamin D, and hypervitaminosis D.

Warning

In case of accidental overdose contact a doctor or poison control center immediately.

Hypersensitivity to vitamin D may be a causative factor in infants with idiopathic hypercalcemia. In these children, vitamin D must be strictly restricted.

Caution

Adequate dietary calcium is necessary for response to vitamin D therapy.

Side Effects

Metabolic side effects include hypercalcemia.

You may report serious side effects by calling Virtus at 1-888-848-3593 or FDA at 1-800-FDA-1088

How Supplied

Each 60 mL polycarbonate screw top bottle contains 60 mL ergocalciferol in a propylene glycol base (0.2 mg ergocalciferol per mL).

Store at 20˚-25˚ C (68˚-77˚F); excursion permitted between 15˚-30˚ C (59˚-86˚ F).

HEALTH CLAIM

Adequate intake (AI) (minimum daily intake) of vitamin D is needed to support calcium metabolism and bone health, particularly in the young and old. [This statement has not been evaluated by the FDA. This product is not intended to diagnose, treat, cure, or prevent any disease.]

SAFE HANDLING WARNING

KEEP THIS AND ALL
MEDICATIONS OUT OF THE
REACH OF CHILDREN.

Tamper Resistant Feature:
Do NOT use if imprinted seal on cap is broken or missing.

HEALTH CLAIM

Manufactured for:
Virtus Pharmaceuticals, LLC
Tampa, FL 33619
1-888-848-3593
Made in USA

7274
Rev. 09/15

PRINCIPAL DISPLAY PANEL - 60 mL Bottle Carton

VIRTUS
PHARMACEUTICALS

69543-234-60

Ergocalciferol
Oral Solution, USP

Vitamin D Supplement Drops
8000 IU (0.2mg) Ergocalciferol per mL

60 mL (2 fl. oz.)